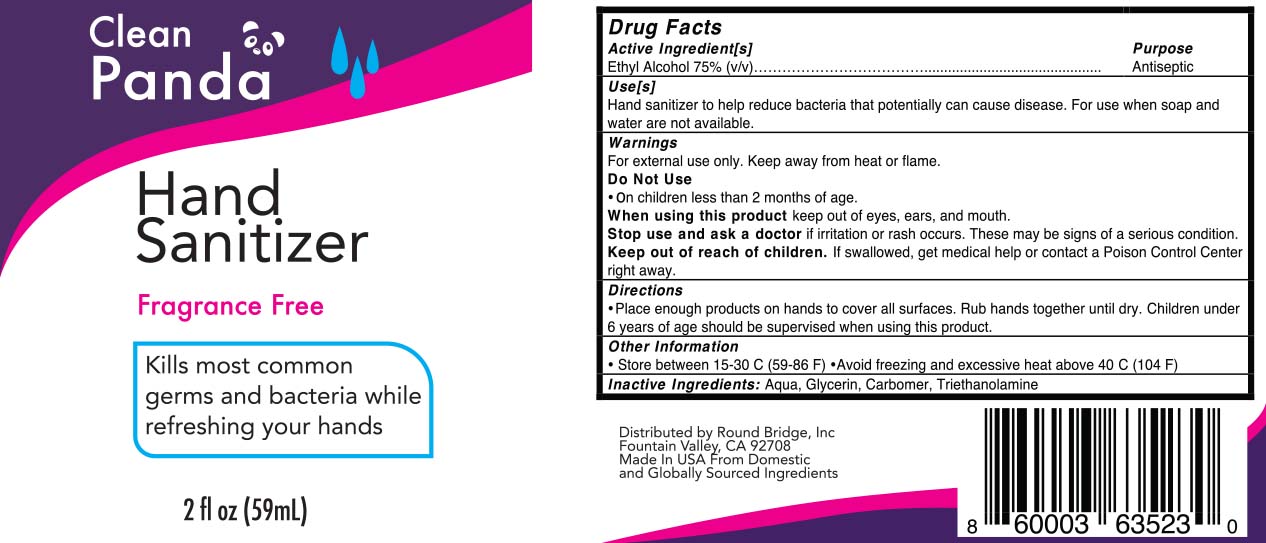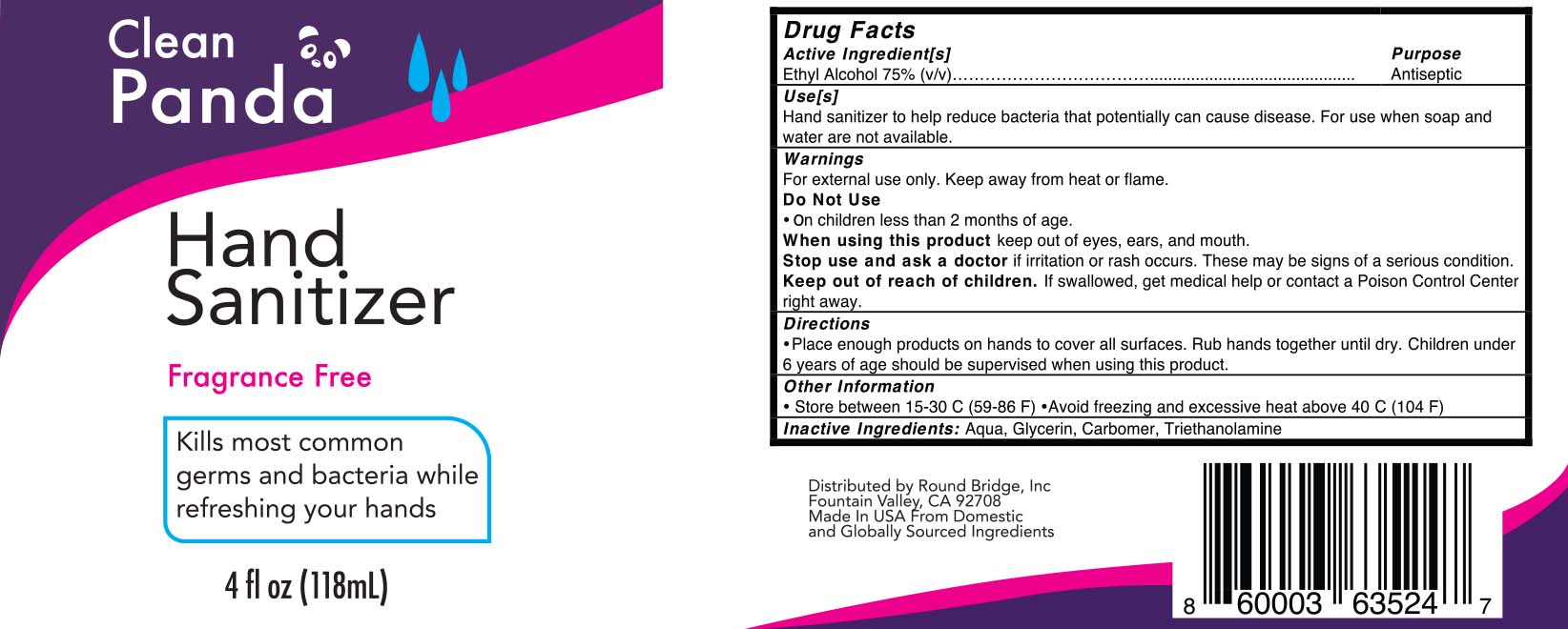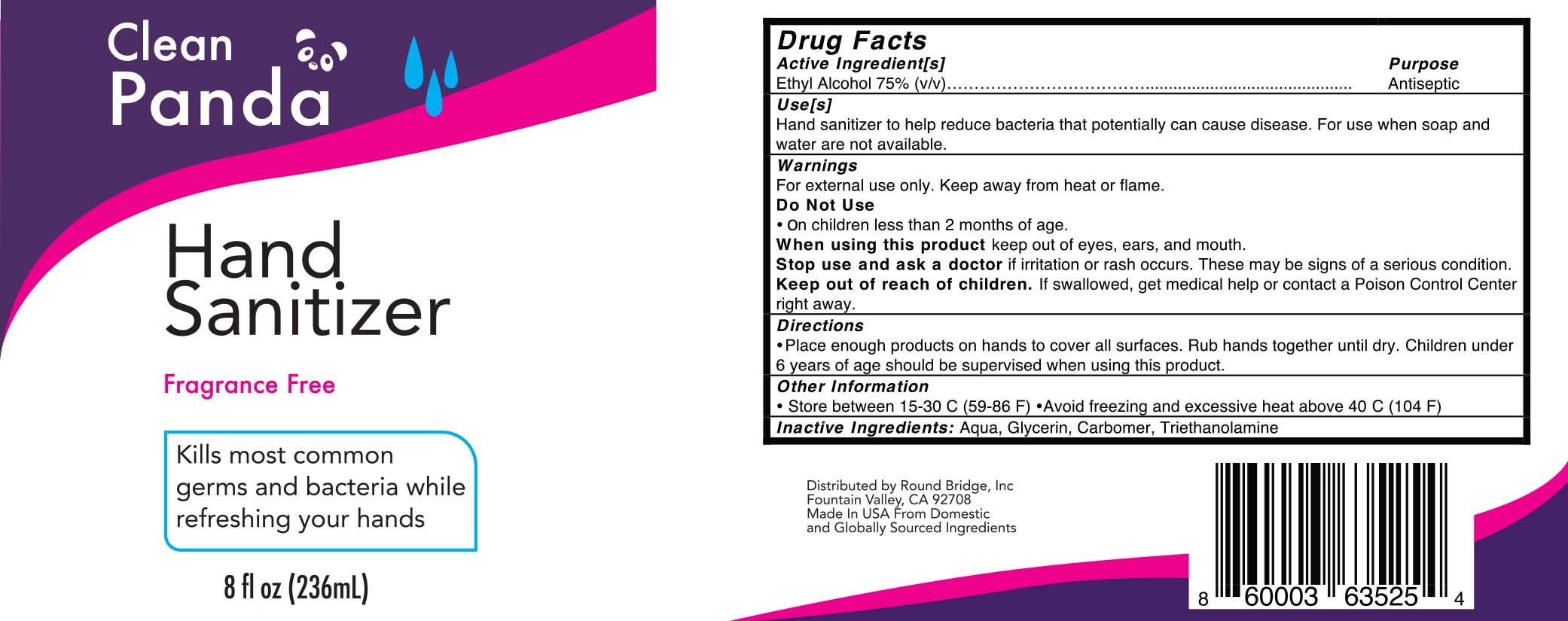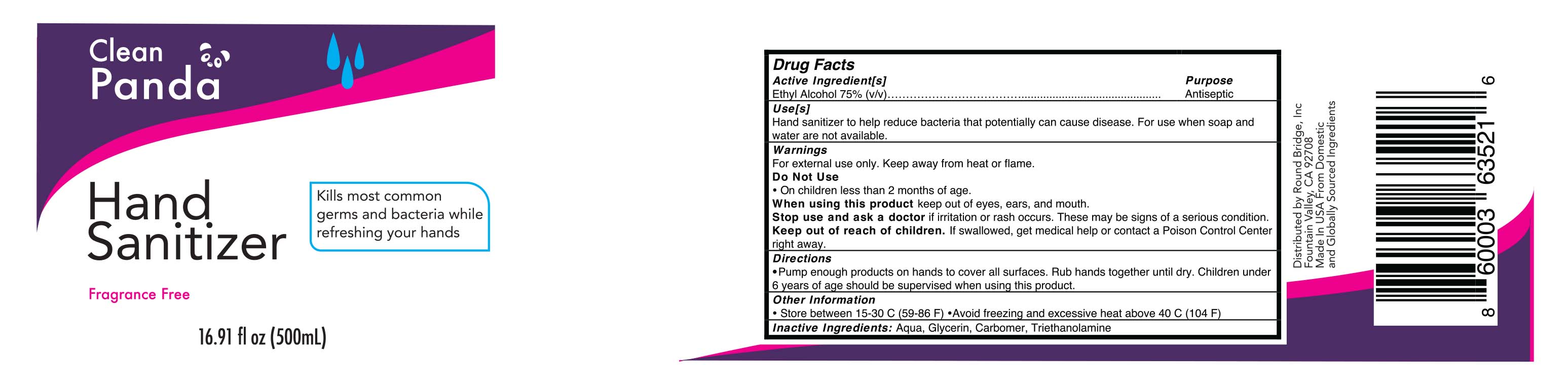 DRUG LABEL: Hand Sanitizer
NDC: 34839-003 | Form: GEL
Manufacturer: Round Bridge Inc
Category: otc | Type: HUMAN OTC DRUG LABEL
Date: 20200520

ACTIVE INGREDIENTS: ALCOHOL 75 mL/100 mL
INACTIVE INGREDIENTS: POLYACRYLIC ACID (8000 MW) 0.25 mL/100 mL; TROLAMINE 0.25 mL/100 mL; GLYCERIN 1 mL/100 mL; WATER

Hand Sanitizer

Active Ingredient(s)

Ethyl Alcohol 75% v/v. Purpose: Antiseptic

Purpose

Antiseptic, Hand Sanitizer

Use

Hand Sanitizer to help reduce bacteria that potentially can cause disease. For use when soap and water are not available.

Warnings

For external use only. Keep away from heat or flame

Do not use

- in children less than 2 months of age

When using this product keep out of eyes, ears, and mouth.

Stop use and ask a doctor if irritation or rash occurs. These may be signs of a serious condition.

Keep out of reach of children. If swallowed, get medical help or contact a Poison Control Center right away.

Directions

- Place enough product on hands to cover all surfaces. Rub hands together until dry.
- Children under 6 years of age should be supervised when using this product.

Other information

- Store between 15-30C (59-86F)
- Avoid freezing and excessive heat above 40C (104F)

Inactive ingredients

Aqua, Glycerin, Carbomer, Triethanolamine

Package Label - Principal Display Panel

59 ml NDC: 34839-002-01

118 ml NDC: 34839-002-02

236 ml NDC: 34839-002-03

500 ml NDC: 34839-002-04